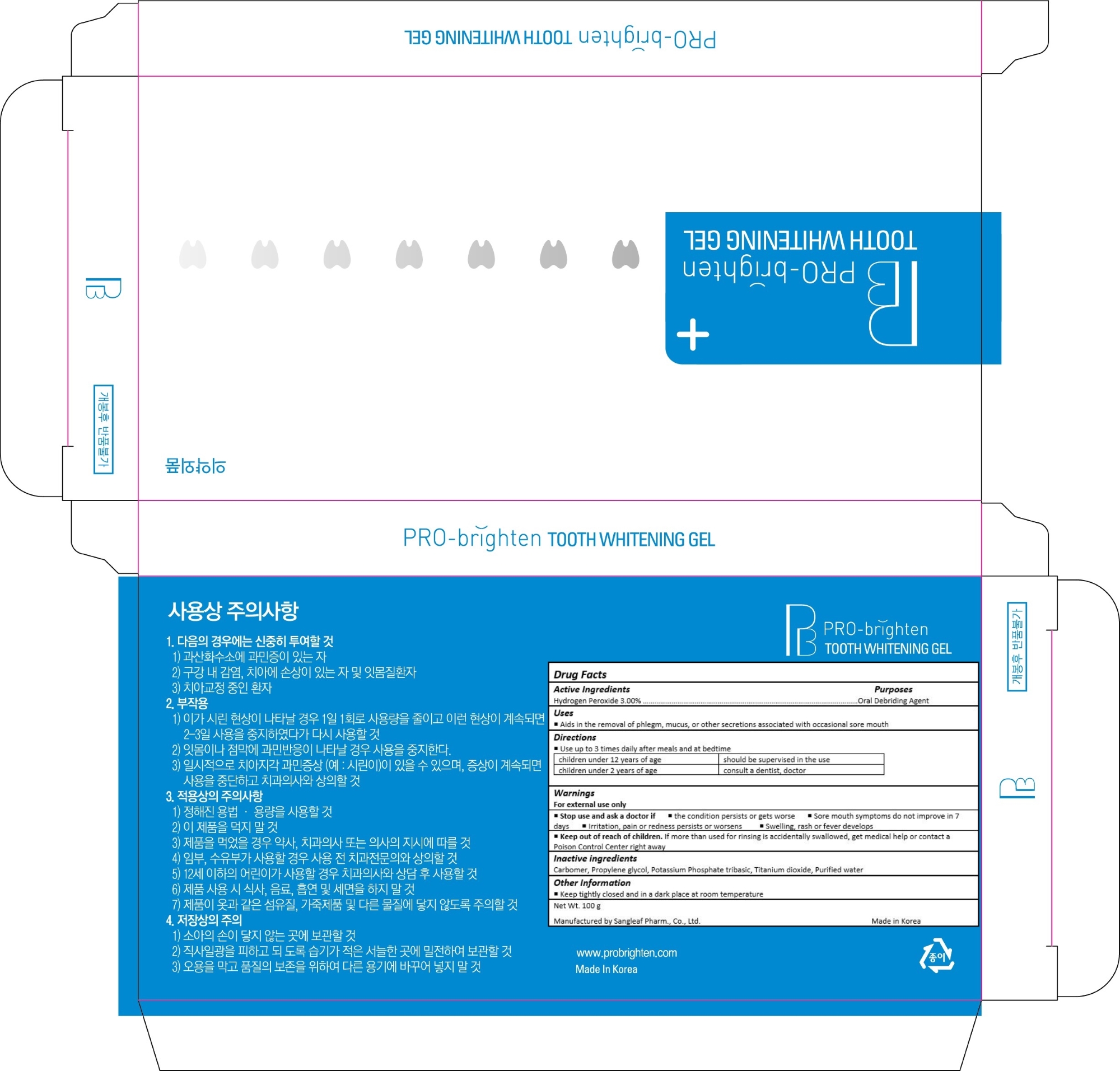 DRUG LABEL: Pro Brighten Tooth whitening Gel
NDC: 70810-001 | Form: GEL
Manufacturer: Sangleaf Pharm., Co Ltd
Category: otc | Type: HUMAN OTC DRUG LABEL
Date: 20160706

ACTIVE INGREDIENTS: Hydrogen Peroxide 3 g/100 g
INACTIVE INGREDIENTS: CARBOXYPOLYMETHYLENE; PROPYLENE GLYCOL; POTASSIUM PHOSPHATE, TRIBASIC; TITANIUM DIOXIDE; WATER

Drug Facts

ACTIVE INGREDIENT

Hydrogen Peroxide 3.00%

PURPOSE

Oral Debriding

INDICATIONS AND USAGE

Aids in the removal of phlegm, mucus, or other secretions associated with occasional sore mouth

DOSAGE AND ADMINISTRATION

Use up to 3 times daily after meals and at bedtime

children under 12 years of age: should be supervised in the use

children under 2 years of age: consult a dentist, doctor

WARNINGS

For external use only

ASK DOCTOR

The condition persists or gets worse

Sore mouth symptoms do not improve in 7 days

Irritation, pain or redness persists or worsens

Swelling, rash or fever develops

Keep out of reach of children. If more than used for rinsing is accidentally swallowed, get medical help or contact a Poison Control Center right away

INACTIVE INGREDIENT

Carbomer, Propylene glycol, Potassium Phosphate tribasic, Titanium dioxide, Purified water